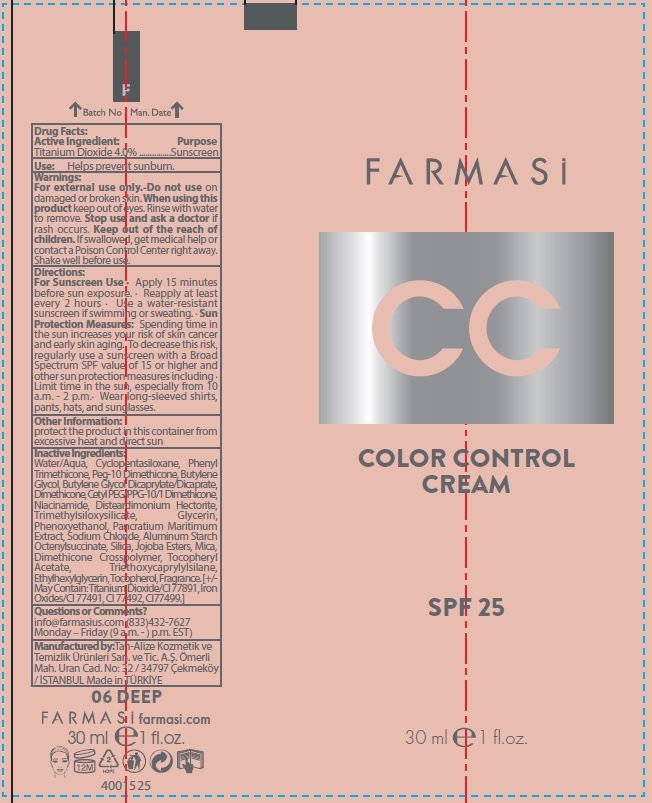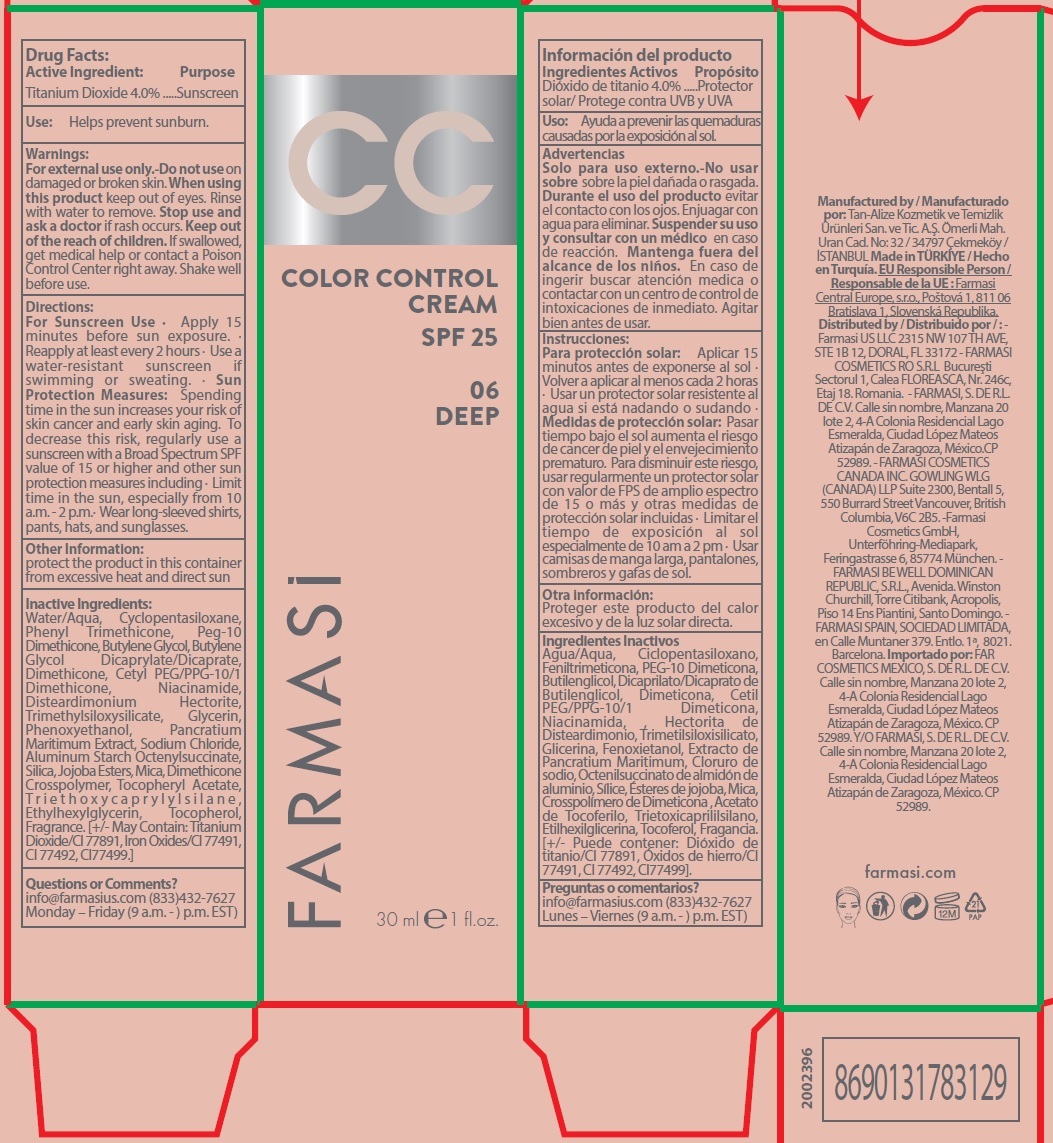 DRUG LABEL: Farmasi CC Color Control Cream SPF 25- 06 Deep
NDC: 74690-051 | Form: CREAM
Manufacturer: Farmasi US LLC
Category: otc | Type: HUMAN OTC DRUG LABEL
Date: 20231105

ACTIVE INGREDIENTS: TITANIUM DIOXIDE 40 mg/1 mL
INACTIVE INGREDIENTS: WATER; CYCLOMETHICONE 5; PHENYL TRIMETHICONE; BUTYLENE GLYCOL; BUTYLENE GLYCOL DICAPRYLATE/DICAPRATE; DIMETHICONE; NIACINAMIDE; DISTEARDIMONIUM HECTORITE; GLYCERIN; PHENOXYETHANOL; SODIUM CHLORIDE; ALUMINUM STARCH OCTENYLSUCCINATE; SILICON DIOXIDE; MICA; .ALPHA.-TOCOPHEROL ACETATE; TRIETHOXYCAPRYLYLSILANE; ETHYLHEXYLGLYCERIN; TOCOPHEROL

Farmasi CC Color Control Cream SPF 25- 06 Deep

Active Ingredient:

Titanium Dioxide 4.0%

Purpose

Sunscreen

Use:

Helps prevent sunburn.

Warnings:

For external use only.

Do not use

- on damaged or broken skin.

When using this product

keep out of eyes. Rinse with water to remove.

Stop use and ask a doctor

if rash occurs.

Keep out of the reach of children.

If swallowed, get medical help or contact a Poison Control Center right away. Shake well before use.

Directions:

· Apply 15 minutes before sun exposure. · Spending time in the sun increases your risk of skin cancer and early skin aging. To decrease this risk, regularly use a sunscreen with a Broad Spectrum SPF value of 15 or higher and other sun protection measures including · Limit time in the sun, especially from 10 a.m. - 2 p.m.· Wear long-sleeved shirts, pants, hats, and sunglasses. For Sunscreen Use Sun Protection Measures:

Other Information:

protect the product in this container from excessive heat and direct sun

Inactive Ingredients:

Water/Aqua, Cyclopentasiloxane, Phenyl Trimethicone, Peg-10 Dimethicone, Butylene Glycol, Butylene Glycol Dicaprylate/Dicaprate, Dimethicone, Cetyl PEG/PPG-10/1 Dimethicone, Niacinamide, Disteardimonium Hectorite, Trimethylsiloxysilicate, Glycerin, Phenoxyethanol, Pancratium Maritimum Extract, Sodium Chloride, Aluminum Starch Octenylsuccinate, Silica, Jojoba Esters, Mica, Dimethicone Crosspolymer, Tocopheryl Acetate, Tr i e t h o x y c a p r y l y l s i l a n e , Ethylhexylglycerin, Tocopherol, Fragrance. [+/- May Contain: Titanium Dioxide/CI 77891, Iron Oxides/CI 77491, CI 77492, CI77499.]

Questions or Comments?

info@farmasius.com (833)432-7627 Monday – Friday (9 a.m. -) p.m. EST)